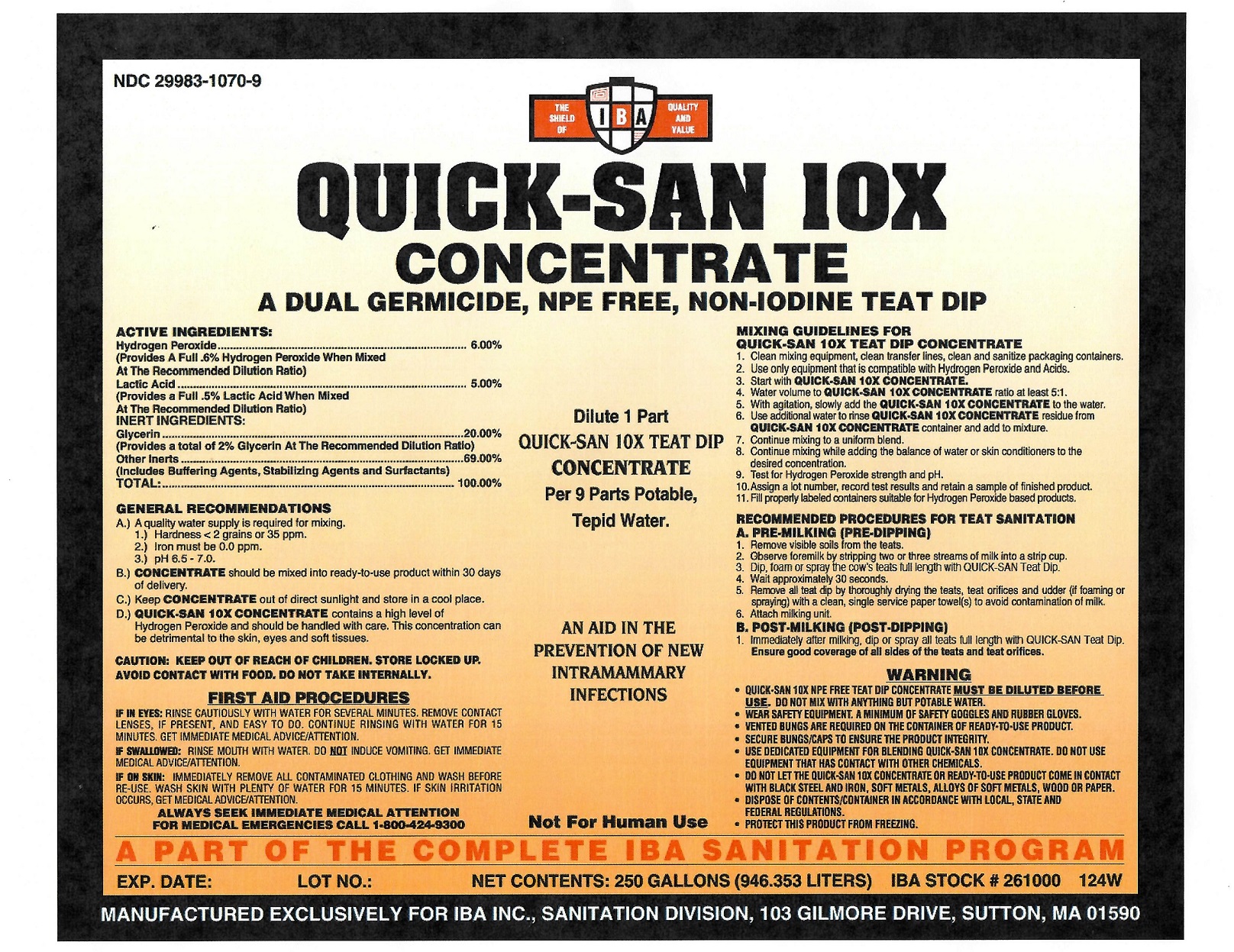 DRUG LABEL: Quick-San 10X Concentrate
NDC: 29983-1070 | Form: LIQUID
Manufacturer: IBA
Category: animal | Type: OTC ANIMAL DRUG LABEL
Date: 20251211

ACTIVE INGREDIENTS: HYDROGEN PEROXIDE 6 kg/100 kg; LACTIC ACID 5 kg/100 kg

Quick-San 10X Concentrate

ACTIVE INGREDIENT

Hydrogen Peroxide..........................................................6.00%

(Provides A Full .6% Hydrogen Peroxide When Mixed At The Recommended Dilution Ratio)

Lactic Acid......................................................................5.00%

(Provides A Full .5% Lactic Acid When Mixed At The Recommended Dilution Ratio)

INERT INGREDIENTS

Glycerin................................................................... .....20.00%

(Provides A Total 2% Glycerin At The Recommended Dilution Ratio)

Other Inerts...................................................................69.00%

(Includes Buffering Agents, Stabilizing Agents, and Surfactants)

TOTAL...................................................................... ..100.00%

GENERAL RECOMMENDATIONS

A.) A quality water supply is required for mixing.
1.) Hardness <2 grains or 35 ppm
2.) Iron must be 0.0 ppm
3.) pH 6.5-7.0
B.) CONCENTRATE should be mixed into ready-to-use product within 30 days of delivery,
C.) Keep CONCENTRATE out of direct sunlight and store in a cool place
D.) QUICK-SAN 10X CONCENTRATE contains a high level of Hydrogen Peroxide and should be handled with care. This concentration can be detrimental to the skin, eyes and soft tissues.

FIRST AID PROCEDURES

IF IN EYES: RINSE CAUTIOUSLY WITH WATER FOR SEVERAL MINUTES. REMOVE CONTACT LENSES, IF PRESENT, AND EASY TO DO. CONTINUE RINSING WITH WATAER FOR 15 MINUTES. GET IMMEDIATE MEDICAL ADVICE/ATTENTION.

IF SWALLOWED: RINSE MOUTH WITH WATER. DO NOTH INDUCE VOMITING. GET IMMEDIATE MEDICAL ADVICE/ATTENTION.

IF ON SKIN: IMMEDIATELY REMOVE ALL CONTAMINATED CLOTHING AND WASH BEFORE RE-USE. WASH SKIN WITH PLENTY OF WATER FOR 15 MINUTES. IF SKIN IRRITATION OCCURS, GET MEDICAL ADVICE/ATTENTION

ALWAYS SEEK IMMEDIATE MEDICAL ATTENTION
FOR MEDICAL EMERGENCIES CALL 1-800-424-9300

MIXING GUIDELINES FOR QUICK- SAN 10X TEAT DIP CONCENTRATE

1. Clean mixing equipment, clean transfer lines, clean and sanitize packing containers.
2. Use only equipment that is compatible with Hydrogen Peroxide and Acids.
3. Start with QUICK- SAN 10X CONCENTRATE.
4. Water volume to QUICK- SAN 10X CONCENTRATE ratio at least 5:1.
5. With agitation, slowly add the QUICK- SAN 10X CONCENTRATE to the water.
6. Use additional water to rinse QUICK- SAN 10X CONCENTRATE residue from QUICK- SAN 10X CONCENTRATE container and add to mixture.
7. Continue mixing to a uniform blend.
8. Continue mixing while adding the balance of water or skin conditioners to the desired concentration.
9. Test for Hydrogen Peroxide strength pH.
10. Assign a lot number , record test results and retain a sample of finished product.
11. Fill properly labeled containers suitable for Hydrogen Peroxide based products.

CAUTION: KEEP OUT OF REACH OF CHILDREN, STORE LOCKED UP.
AVOID CONTACT WITH FOOD. DO NOT TAKE INTERNALLY.

DILUTE 1 PART
QUICK- SAN 10X TEAT DIP
CONCENTRATE
Per 9 Parts Potable,
Tepid Water.

AN AID IN THE
PREVENTION OF NEW
INTRAMAMMARY
INFECTIONS

WARNING

- QUICK-SAN 10X NPE FREE TEAT DIP CONCENTRATE MUST BE DILUTED BEFORE USE. DO NOT MIX WITH ANYTHING BUT POTABLE WATER.
- WEAR SAFETY EQUIPMENT. A MINIMUM OF SAFETY GOGGLES AND RUBBER GLOVES.
- VENTED BUNGS ARE REQUIRED ON THE CONTAINER OF READY-TO-USE PRODUCT.
- SECURE BUNGS/CAPS TO ENSURE THE PRODUCT INTEGRITY.
- USE DEDICATED EQUIPMENT FOR BLENDING QUICK-SAN 10X CONCENTRATE. DO NOT USE EQUIPMENT THAT HAS CONTACT WITH OTHER CHEMICALS.
- DO NOT LET THE QUICK-SAN 10X CONCENTRATE OR READY-TO-USE PRODUCT COME INTO CONTACT WITH BLACK STEEL AND IRON, SOFT METALS, ALLOYS OF SOFT METALS, WOODOR PAPER.
- DISPOSE OF CONTENTS/CONTAINER IN ACCORDANCE WITH LOCAL, STATE AND FEDERAL REGULATIONS.
- PROTECT THIS PRODUCT FROM FREEZING